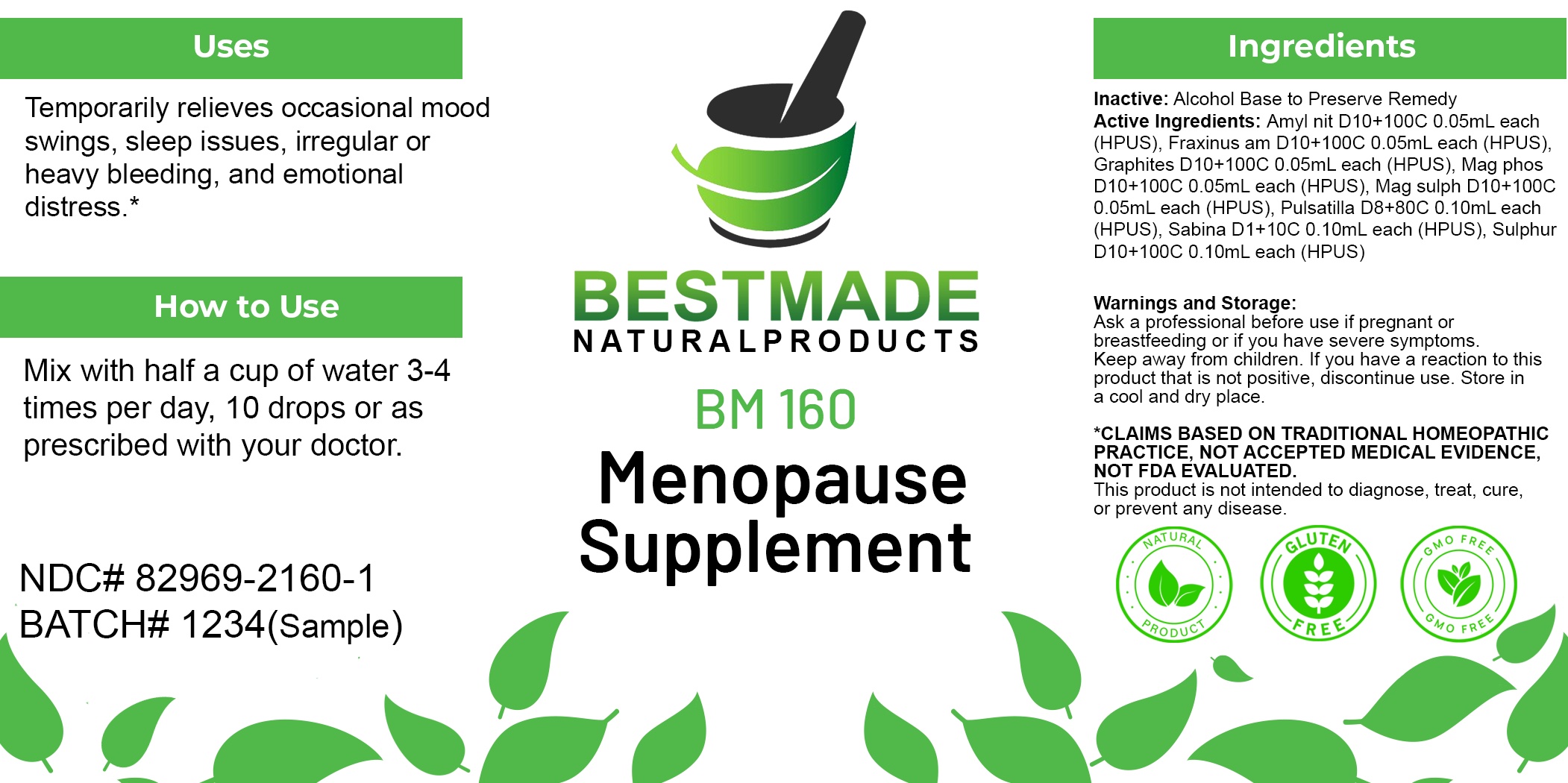 DRUG LABEL: Bestmade Natural Products BM160
NDC: 82969-2160 | Form: LIQUID
Manufacturer: Bestmade Natural Products
Category: homeopathic | Type: HUMAN OTC DRUG LABEL
Date: 20250218

ACTIVE INGREDIENTS: MAGNESIUM PHOSPHATE, DIBASIC TRIHYDRATE 30 [hp_C]/30 [hp_C]; JUNIPERUS SABINA LEAFY TWIG 30 [hp_C]/30 [hp_C]; SULFUR 30 [hp_C]/30 [hp_C]; MAGNESIUM SULFATE HEPTAHYDRATE 30 [hp_C]/30 [hp_C]; AMYL NITRITE 30 [hp_C]/30 [hp_C]; PULSATILLA PRATENSIS 30 [hp_C]/30 [hp_C]; GRAPHITE 30 [hp_C]/30 [hp_C]; FRAXINUS AMERICANA BARK 30 [hp_C]/30 [hp_C]
INACTIVE INGREDIENTS: ALCOHOL 30 [hp_C]/30 [hp_C]

BM160

ACTIVE INGREDIENT

ACTIVE INGREDIENTS: Amyl nit D10+100C 0.05mL each (HPUS), Fraxinus am D10+100C 0.05mL each (HPUS), Graphites D10+100C 0.05mL each (HPUS), Mag phos D10+100C 0.05mL each (HPUS), Mag sulph D10+100C 0.05mL each (HPUS), Pulsatilla D8+80C 0.10mL each (HPUS), Sabina D1+10C 0.10mL each (HPUS), Sulphur D10+100C 0.10mL each (HPUS)

Inactive:

Alcohol Base to Preserve Product

DOSAGE AND ADMINISTRATION

How to Use

Mix with half a cup of water 3-4 times per day. Ages 12 or older, 10 drops. Ages 12-2, 5 drops. Ages 2 and under, consult your Doctor.

Uses
Temporarily relieves occasional mood swings, sleep issues, irregular or heavy bleeding, and emotional distress.*

Uses
Temporarily relieves occasional mood swings, sleep issues, irregular or heavy bleeding, and emotional distress.*

KEEP OUT OF REACH OF CHILDREN

Warnings and Storage:

Ask a professional before use if pregnant or breastfeeding or if you have severe symptoms.

Keep away from children. If you have a reaction to this product that is not positive, discontinue use. Store in a cool and dry place

*CLAIMS BASED ON TRADITIONAL HOMEOPATHIC PRACTICE, NOT ACCEPTED MEDICAL EVIDENCE NOT FDA EVALUATED.
This product is not intended to diagnose, treat, cure, or prevent any disease.

Warnings and Storage:

Ask a professional before use if pregnant or breastfeeding or if you have severe symptoms.

Keep away from children. If you have a reaction to this product that is not positive, discontinue use. Store in a cool and dry place

*CLAIMS BASED ON TRADITIONAL HOMEOPATHIC PRACTICE, NOT ACCEPTED MEDICAL EVIDENCE NOT FDA EVALUATED.
This product is not intended to diagnose, treat, cure, or prevent any disease.

Entire package label